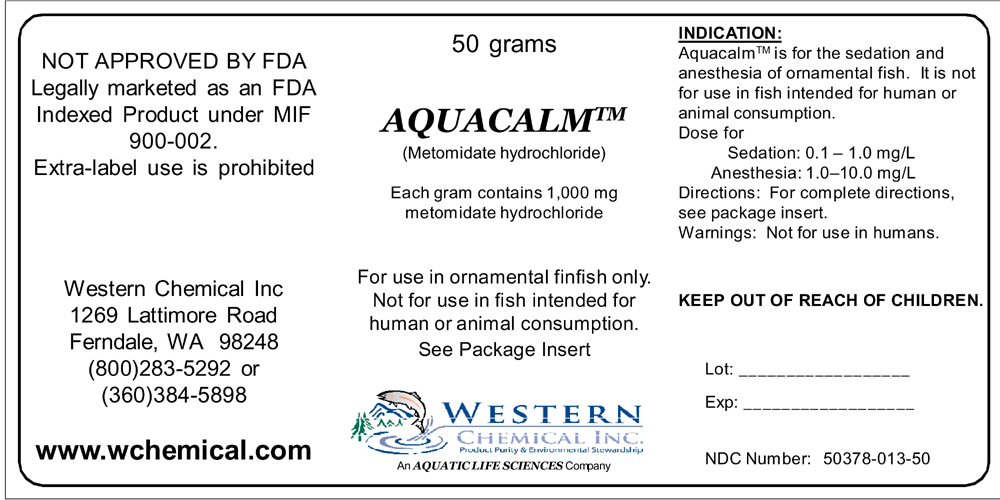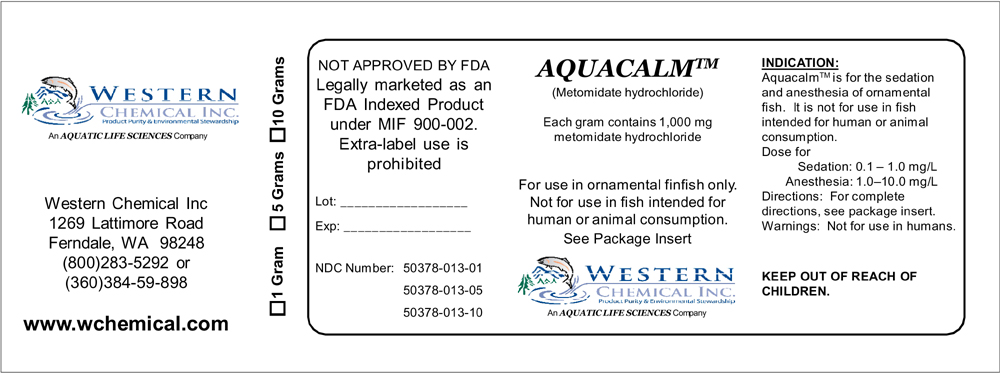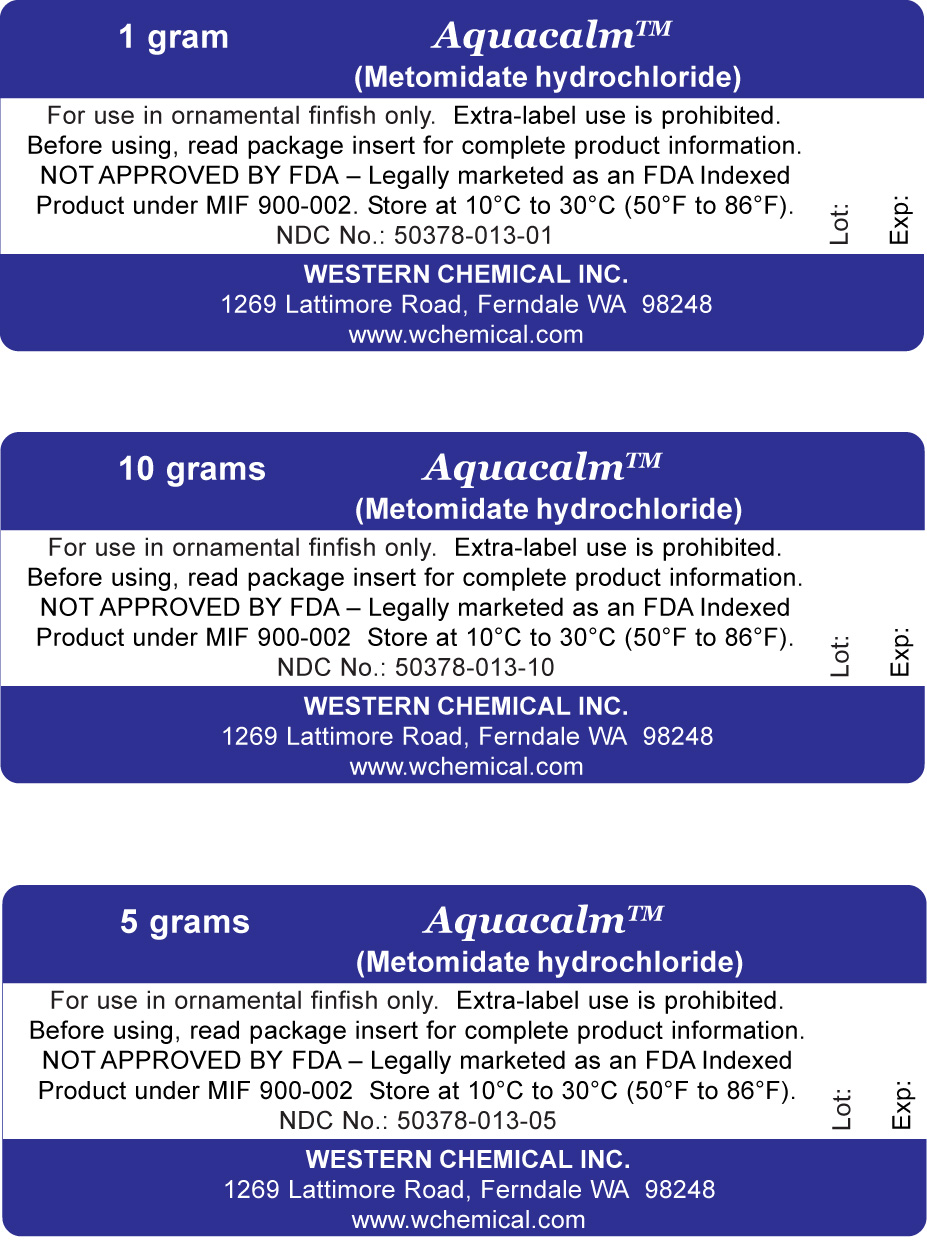 DRUG LABEL: Aquacalm
NDC: 50378-013 | Form: POWDER
Manufacturer: Western Chemical Inc.
Category: animal | Type: OTC ANIMAL DRUG LABEL
Date: 20120919

ACTIVE INGREDIENTS: metomidate 1000 mg/1 g

AquacalmTM (Metomidate hydrochloride) For immersion use in ornamental finfish only. Not for use in fish intended for human or animal consumption. NOT APPROVED BY FDA – Legally marketed as an FDA indexed product under MIF 900-002. Extra-label use is prohibited. Note--In order to be legally marketed, an animal drug product intended for a minor species must be Approved, Conditionally Approved, or Indexed. THIS PRODUCT IS INDEXED. It is a violation of Federal law to use this product in a manner other than as directed in the labeling. As used on this label, the words "ornamental fish" refer to a wide variety of finfish species maintained primarily for their appearance and do not include any fish that are consumed by humans or food-producing animals.

DESCRIPTION

NET CONTENTS: 1, 5, 10 or 50 grams

DESCRIPTION: Each gram of AquacalmTM powder contains 1 gm of metomidate hydrochloride. AquacalmTM acts on the central nervous system to induce sedation or anesthesia in fish immersed in water containing the drug.

INDICATIONS AND USAGE

INDICATION: For the sedation and anesthesia of ornamental finfish. AquacalmTM is not for use in fish intended for human or animal consumption. Sedation may be necessary in
situations such as strip spawning for hatchery rearing, transporting fish from supplier to wholesaler or retailer, photographing fish as part of a strategic marketing approach, or removal of fish from exhibit tanks prior to cleaning. Anesthesia may be necessary in situations where detailed fish examination or minor surgical procedures are to be conducted.

WARNINGS AND PRECAUTIONS

CAUTION:
FOR USE IN ORNAMANTAL FINFISH ONLY.
NOT FOR USE IN FISH INTENDED FOR HUMAN OR ANIMAL CONSUMPTION.
WARNING:
Not for use in humans. Keep out of the reach of children. Use in a well-ventilated area. Wear gloves.

INHALATION: May be harmful. Remove immediately from danger zone and provide fresh air. In case of respiratory problems or respiratory arrest, administer artificial respiration. Keep the affected individual warm and still. Contact emergency medical help.

INGESTION: May be harmful. If the person is conscious, wash out mouth with copious amounts of water. Contact emergency medical help.

EYE CONTACT: May be harmful. In case of contact, flush with copious amounts of water for at least 15 minutes. Assure
adequate flushing by separating eyelids with fingers. Contact emergency medical help.

SKIN CONTACT: May be harmful. In case of contact, flush with copious amounts of water for at least 15 minutes. Remove
contaminated clothing and wash before re-using. Contact emergency medical help.

OTHER HEALTH INFORMATION: The toxicological properties of metomidate hydrochloride have not been thoroughly investigated. It is thought to act on the central nervous system as an imidazole based non-barbiturate hypnotic.

To obtain a Material Safety Data Sheet, call WESTERN CHEMICAL INC. at (360) 384-5898, or visit www.wchemical.com

DOSAGE AND ADMINISTRATION

DIRECTIONS FOR USE:
AquacalmTM is packaged as a dry powder and must be mixed with water to be used. Determine the amount of AquacalmTM powder needed to achieve the desired concentration for the intended use. Dissolve AquacalmTM in a known volume of water, mix well, and aerate water during sedation or anesthesia. Lightly sedated fish may lose their ability to maintain upright position or position in a stream flow. Deeply sedated or anesthetized fish will experience total loss of equilibrium. Before beginning sedation or anesthesia, ensure that AquacalmTM-free water is available for recovery. Always test the dosage on a small group of fish first to make sure no unintended or adverse effects occur.
SPECIES:
AquacalmTM has been tested on representative ornamental finfish species, but has not been tested on all fish species. The effect of AquacalmTM may vary between (and within) species, depending upon age and physical condition of fish, and under different water conditions. Sedate or anesthetize fish in water with temperature and pH close to the temperature and pH of the rearing water.
Caution should be taken when using this product on/for:
1. Larval fish species, which may be more sensitive to sedation than older fish of the same species
2. Fish species such as knifefish and gouramis
3. Any fish species for extended periods (e.g.> 24 hr) used during transportation
DOSAGE:
Dose for sedation: 0.1 to 1.0 mg/L
Dose for anesthesia: 1.0 to 10.0 mg/L
The dose should be individualized, depending upon the fish species and the degree of anesthesia required. Consideration should be taken when sedating or anesthetizing fish at water temperatures substantially different from the species preferred water temperature or at very low pH.
DURATION OF TREATMENT:
At doses suitable for total loss of equilibrium or anesthesia, do not expose fish for more than 60 min. At doses suitable to sedate fish for transportation, do not expose fish for more than 24 hr. To facilitate recovery upon removal from a solution of AquacalmTM, place fish in well oxygenated, high quality water free of AquacalmTM. Fish should recover in 20 to 90 min.
CONTRAINDICATIONS:
Use of AquacalmTM is contraindicated in species of fish that rely upon accessory air breathing organs for oxygen consumption. Sedation or anesthesia of such species may result in unacceptable rates of mortality.
DOSE CALCULATION:
The dose is based on the volume of water in which fish will be placed or held.
For example, if the desired AquacalmTM concentration is 2.0 mg/L and the tank holding the fish contains 10 L of water, use the following calculation:
2 mg/L X 10L = 20 mg = 0.02 g AquacalmTM
For example, if the desired AquacalmTM concentration is 2.0 mg/L and the tank holding the fish contains 5 gal of water, use the following calculation (note that the correction factor is used when volume is reported in gallons):
2 mg/L X 5 gal X 0.00378 = 0.038 g AquacalmTM

STORAGE and HANDLING:
Store at 10°C to 30°C (50°F to 86°F) and protect from sunlight and sources of heat.
DISPOSAL:
Contact your State Environmental Control Agency, or the Hazardous Waste Representative at the nearest EPA Regional Office for guidance pertaining to disposal of unused product.
QUESTIONS/COMMENTS? For technical assistance, call Western Chemical Inc. at (360) 384-5898. To report an adverse event, call WESTERN CHEMICAL INC. at (360) 384-5898, or FDA at 1-888-FDA-VETS.